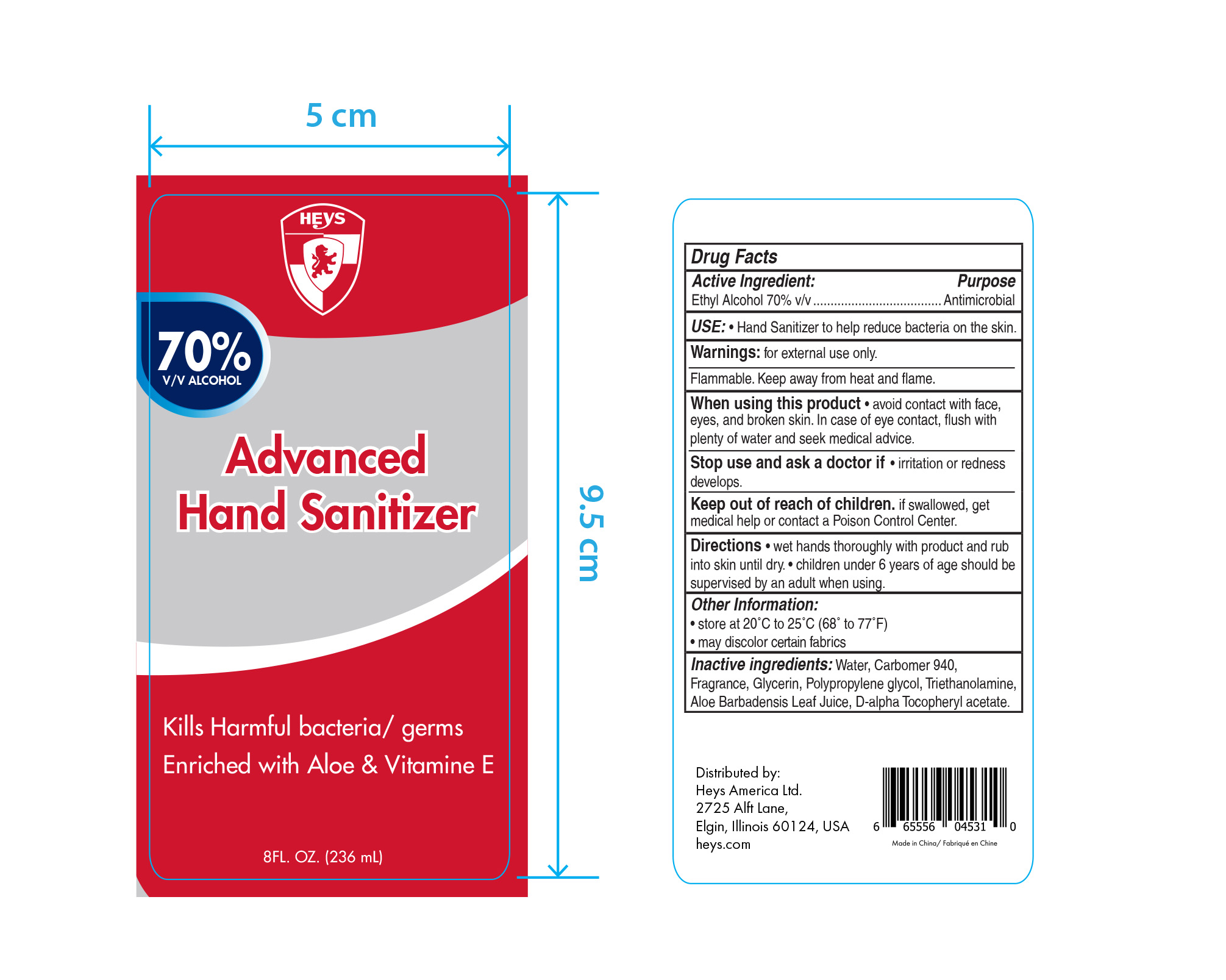 DRUG LABEL: Heys Hand Sanitizer
NDC: 77404-001 | Form: GEL
Manufacturer: Heys America Ltd.
Category: otc | Type: HUMAN OTC DRUG LABEL
Date: 20200505

ACTIVE INGREDIENTS: ALCOHOL 70 mL/100 mL
INACTIVE INGREDIENTS: CARBOMER 940; TROLAMINE; .ALPHA.-TOCOPHEROL ACETATE, D-; WATER; ALOE VERA LEAF; GLYCERIN; PROPYLENE GLYCOL

Heys Hand Sanitizer

Heys Hand Sanitizer

Ethyl Alcohol 70% v/v

Heys Hand Sanitizer

Antimicrobial

Heys Hand Sanitizer

Use: Hand Sanitizer to help reduce bacteria on the skin.

Heys Hand Sanitizer

Warnings: For external use only

Flammable: Keep away from heat and flame.

Heys Hand Sanitzer

When using this product avoid contact with face, eyes, and broken skin. In case of eye contact, flush with plenty of water and seek medical advice.

Heys Hand Sanitizer

Stop use and ask a a doctor if irritation or redness develops.

Heys Hand Sanitizer

Keep out of reah of children. If swallowed, get medical help or contact a Poison Control Center.

Heys Hand Sanitizer

Directions: wet hands thoroughly with product and rub into skin until dry. children under 6 years of age should be supervised by an adult when using.

Heys Hand Sanitizer

Store at 20 C to 25 C (68 to 77 F)

May discolor certain fabrics

Heys Hand Sanitizer

Water

Carbomer 940

Fragrance

Glycerin

Polypropylene glycol

Triethanolamine

Aloe Barbadensis Leaf Juice

D-alpha Tocopheryl acetate

Heys Hand Sanitizer

236 mL NDC: 77404-001-08